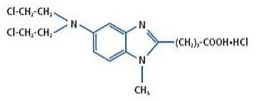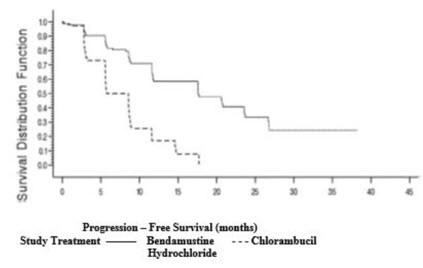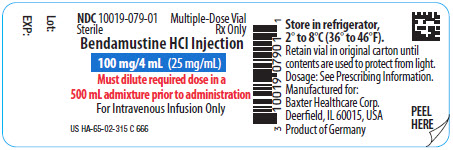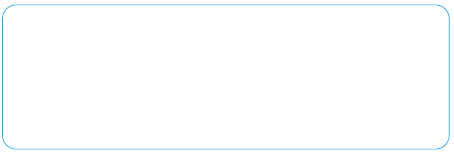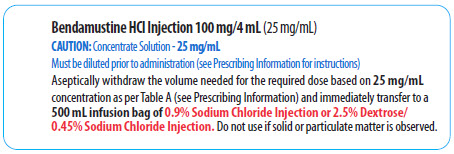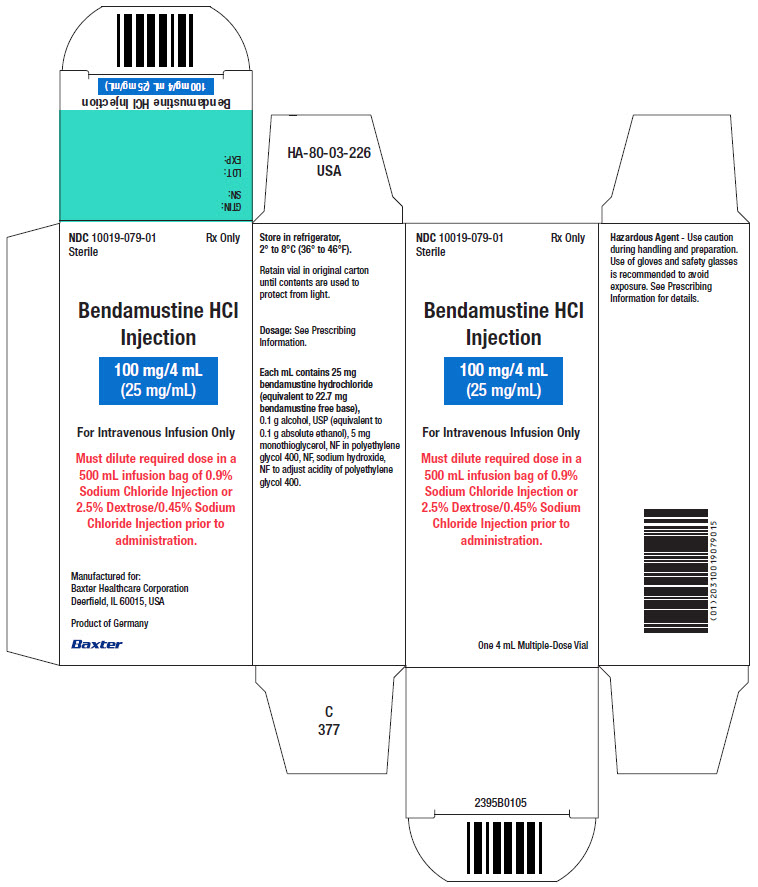 DRUG LABEL: BENDAMUSTINE HYDROCHLORIDE
NDC: 10019-079 | Form: INJECTION
Manufacturer: Baxter Healthcare Corporation
Category: prescription | Type: HUMAN PRESCRIPTION DRUG LABEL
Date: 20250210

ACTIVE INGREDIENTS: BENDAMUSTINE HYDROCHLORIDE 100 mg/1 1
INACTIVE INGREDIENTS: ALCOHOL; MONOTHIOGLYCEROL; POLYETHYLENE GLYCOL 400; SODIUM HYDROXIDE

HIGHLIGHTS OF PRESCRIBING INFORMATION

These highlights do not include all the information needed to use BENDAMUSTINE HYDROCHLORIDE INJECTION safely and effectively. See full prescribing information for BENDAMUSTINE HYDROCHLORIDE INJECTION.
BENDAMUSTINE HYDROCHLORIDE injection, for intravenous use.
Initial U.S. Approval: 2008

1 INDICATIONS AND USAGE

Bendamustine Hydrochloride Injection is an alkylating drug indicated for treatment of adult patients with:

- Chronic lymphocytic leukemia (CLL). Efficacy relative to first line therapies other than chlorambucil has not been established. (1.1)
- Indolent B-cell non-Hodgkin lymphoma (NHL) that has progressed during or within six months of treatment with rituximab or a rituximab-containing regimen. (1.2)

2 DOSAGE AND ADMINISTRATION

For CLL:

- 100 mg/m^2 infused intravenously over 30 minutes on Days 1 and 2 of a 28-day cycle, up to 6 cycles. (2.1)

For NHL:

- 120 mg/m^2 infused intravenously over 60 minutes on Days 1 and 2 of a 21-day cycle, up to 8 cycles. (2.2)

3 DOSAGE FORMS AND STRENGTHS

Injection: 100 mg/4 mL (25 mg/mL) in a multiple-dose vial. (3)

4 CONTRAINDICATIONS

Bendamustine Hydrochloride Injection is contraindicated in patients with a history of a hypersensitivity reaction to bendamustine, polyethylene glycol 400, alcohol, or monothioglycerol. Reactions to bendamustine hydrochloride have included anaphylaxis and anaphylactoid reactions. (4, 5.4)

5 WARNINGS AND PRECAUTIONS

- Myelosuppression: Delay or reduce dose, and restart treatment based on ANC and platelet count recovery. (5.1)
- Infections: Monitor for fever and other signs of infection or reactivation of infections and treat promptly. (5.2)
- Progressive Multifocal Leukoencephalopathy (PML): Monitor for new or worsening neurological, cognitive or behavioral signs or symptoms suggestive of PML. (5.3)
- Anaphylaxis and Infusion Reactions: Severe anaphylactic reactions have occurred. Monitor clinically and discontinue drug for severe reactions. Pre-medicate in subsequent cycles for milder reactions. (5.4)
- Tumor Lysis Syndrome: May lead to acute renal failure and death; anticipate and use supportive measures in patients at high risk. (5.5)
- Skin Reactions: Discontinue for severe skin reactions. Cases of SJS, DRESS and TEN, some fatal, have been reported. (5.6)
- Hepatotoxicity: Monitor liver chemistry tests prior to and during treatment. (5.7)
- Other Malignancies: Pre-malignant and malignant diseases have been reported. (5.8)
- Extravasation Injury: Take precautions to avoid extravasation, including monitoring intravenous infusion site during and after administration. (5.9)
- Embryo-Fetal Toxicity: Can cause fetal harm. Advise females of reproductive potential and males with female partners of reproductive potential of the potential risk to a fetus and to use an effective method of contraception. (5.10, 8.1)

6 ADVERSE REACTIONS

- Adverse reactions (frequency >5%) during infusion and within 24 hours post-infusion are nausea and fatigue. (6.1)
- Most common adverse reactions (≥15%) for CLL are anemia, thrombocytopenia, neutropenia, lymphopenia, leukopenia, hyperbilirubinemia, pyrexia, nausea, vomiting. (6.1)
- Most common adverse reactions (≥15%) for NHL are lymphopenia, leukopenia, anemia neutropenia, thrombocytopenia, nausea, fatigue, vomiting, diarrhea, pyrexia, constipation, anorexia, cough, headache, weight decreased, dyspnea, rash, and stomatitis. (6.1)

To report SUSPECTED ADVERSE REACTIONS, contact Baxter Healthcare Corporation at 1-866-888-2472 or FDA at 1-800-FDA-1088 or http://www.fda.gov/medwatch.

7 DRUG INTERACTIONS

Consider alternative therapies that are not CYP1A2 inducers or inhibitors during treatment with Bendamustine Hydrochloride Injection. (7.1)

8 USE IN SPECIFIC POPULATIONS

- Lactation: Advise not to breastfeed (8.2)
- Infertility: May impair fertility (8.3)
- Renal Impairment: Do not use in patients with creatinine clearance < 30 mL/min (8.6)
- Hepatic Impairment: Do not use in patients with total bilirubin 1.5-3 x ULN and AST or ALT 2.5-10 x ULN, or total bilirubin > 3 x ULN. (8.7)

FULL PRESCRIBING INFORMATION

1 INDICATIONS AND USAGE

1.1 Chronic Lymphocytic Leukemia (CLL)

Bendamustine q Hydrochloride Injection is indicated for the treatment of adult patients with chronic lymphocytic leukemia. Efficacy relative to first line therapies other than chlorambucil has not been established.

1.2 Non-Hodgkin Lymphoma (NHL)

Bendamustine Hydrochloride Injection is indicated for the treatment of adult patients with indolent B-cell non-Hodgkin lymphoma that has progressed during or within six months of treatment with rituximab or a rituximab-containing regimen.

2 DOSAGE AND ADMINISTRATION

2.1 Dosing Instructions for CLL

Recommended Dosage:

The recommended dose is 100 mg/m^2 administered intravenously over 30 minutes on Days 1 and 2 of a 28-day cycle, up to 6 cycles.

Dose Delays, Dose Modifications and Reinitiation of Therapy for CLL:

Delay Bendamustine Hydrochloride Injection administration in the event of Grade 4 hematologic toxicity or clinically significant Grade 2 or greater non-hematologic toxicity. Once non-hematologic toxicity has recovered to less than or equal to Grade 1 and/or the blood counts have improved [Absolute Neutrophil Count (ANC) ≥ 1 x 10^9 /L, platelets ≥ 75 x 10^9 /L], reinitiate Bendamustine Hydrochloride Injection at the discretion of the treating physician. In addition, consider dose reduction. [see Warnings and Precautions (5.1)]

Dose modifications for hematologic toxicity: for Grade 3 or greater toxicity, reduce the dose to 50 mg/m^2 on Days 1 and 2 of each cycle; if Grade 3 or greater toxicity recurs, reduce the dose to 25 mg/m^2 on Days 1 and 2 of each cycle.

Dose modifications for non-hematologic toxicity: for clinically significant Grade 3 or greater toxicity, reduce the dose to 50 mg/m^2 on Days 1 and 2 of each cycle.

Consider dose re-escalation in subsequent cycles at the discretion of the treating physician.

2.2 Dosing Instructions for NHL

Recommended Dosage:

The recommended dose is 120 mg/m^2 administered intravenously over 60 minutes on Days 1 and 2 of a 21-day cycle, up to 8 cycles.

Dose Delays, Dose Modifications and Reinitiation of Therapy for NHL:

Delay Bendamustine Hydrochloride Injection administration in the event of a Grade 4 hematologic toxicity or clinically significant greater or equal to Grade 2 non-hematologic toxicity. Once non-hematologic toxicity has recovered to ≤ Grade 1 and/or the blood counts have improved [Absolute Neutrophil Count (ANC) ≥ 1 x 10^9 /L, platelets ≥ 75 x 10^9 /L], reinitiate Bendamustine Hydrochloride Injection at the discretion of the treating physician. In addition, consider dose reduction. [see Warnings and Precautions (5.1)]

Dose modifications for hematologic toxicity: for Grade 4 toxicity, reduce the dose to 90 mg/m^2 on Days 1 and 2 of each cycle; if Grade 4 toxicity recurs, reduce the dose to 60 mg/m^2 on Days 1 and 2 of each cycle.

Dose modifications for non-hematologic toxicity: for Grade 3 or greater toxicity, reduce the dose to 90 mg/m^2 on Days 1 and 2 of each cycle; if Grade 3 or greater toxicity recurs, reduce the dose to 60 mg/m^2 on Days 1 and 2 of each cycle.

2.3 Preparation for Intravenous Administration

Bendamustine Hydrochloride Injection is a hazardous drug. Follow applicable special handling and disposal procedures.^1

Bendamustine Hydrochloride Injection is in a multiple-dose vial. Bendamustine Hydrochloride Injection is a clear and colorless to yellow solution. Store Bendamustine Hydrochloride Injection at recommended refrigerated storage conditions (2° to 8°C or 36° to 46°F). When refrigerated the contents may partially freeze. Allow the vial to reach room temperature (15° to 30°C or 59° to 86°F) prior to use. Observe the contents of the vial for any visible solid or particulate matter. Do not use the product if solid or particulate matter is observed after reaching room temperature.

Intravenous Infusion

Aseptically withdraw the volume needed for the required dose from the 25 mg/mL solution as per Table A below and immediately transfer to a 500 mL infusion bag of one of the following diluents:

- 0.9% Sodium Chloride Injection, USP; or
- 2.5% Dextrose/0.45% Sodium Chloride Injection, USP.

The resulting final concentration of Bendamustine Hydrochloride Injection in the infusion bag should be within 0.05 to 0.7 mg/mL. After transferring, thoroughly mix the contents of the infusion bag. The admixture should be a clear and colorless to slightly yellow solution.

Use either 0.9% Sodium Chloride Injection, USP, or 2.5% Dextrose/0.45% Sodium Chloride Injection, USP, for dilution, as outlined above. No other diluents have been shown to be compatible.

Table A: Volume (mL) of Bendamustine Hydrochloride Injection required for dilution into 500 mL of 0.9% Sodium Chloride Injection, USP, or 2.5% Dextrose/0.45% Sodium Chloride Injection, USP for a given dose (mg/m^2) and Body Surface Area (m^2)
Body Surface Area (m^2) | Volume of Bendamustine Hydrochloride Injection to withdraw (mL)
Body Surface Area (m^2) | 120 mg/m^2 | 100 mg/m^2 | 90 mg/m^2 | 60 mg/m^2 | 50 mg/m^2 | 25 mg/m^2
1 | 4.8 | 4 | 3.6 | 2.4 | 2 | 1
1.1 | 5.3 | 4.4 | 4 | 2.6 | 2.2 | 1.1
1.2 | 5.8 | 4.8 | 4.3 | 2.9 | 2.4 | 1.2
1.3 | 6.2 | 5.2 | 4.7 | 3.1 | 2.6 | 1.3
1.4 | 6.7 | 5.6 | 5 | 3.4 | 2.8 | 1.4
1.5 | 7.2 | 6 | 5.4 | 3.6 | 3 | 1.5
1.6 | 7.7 | 6.4 | 5.8 | 3.8 | 3.2 | 1.6
1.7 | 8.2 | 6.8 | 6.1 | 4.1 | 3.4 | 1.7
1.8 | 8.6 | 7.2 | 6.5 | 4.3 | 3.6 | 1.8
1.9 | 9.1 | 7.6 | 6.8 | 4.6 | 3.8 | 1.9
2 | 9.6 | 8 | 7.2 | 4.8 | 4 | 2
2.1 | 10.1 | 8.4 | 7.6 | 5 | 4.2 | 2.1
2.2 | 10.6 | 8.8 | 7.9 | 5.3 | 4.4 | 2.2
2.3 | 11 | 9.2 | 8.3 | 5.5 | 4.6 | 2.3
2.4 | 11.5 | 9.6 | 8.6 | 5.8 | 4.8 | 2.4
2.5 | 12 | 10 | 9 | 6 | 5 | 2.5
2.6 | 12.5 | 10.4 | 9.4 | 6.2 | 5.2 | 2.6
2.7 | 13 | 10.8 | 9.7 | 6.5 | 5.4 | 2.7
2.8 | 13.4 | 11.2 | 10.1 | 6.7 | 5.6 | 2.8
2.9 | 13.9 | 11.6 | 10.4 | 7 | 5.8 | 2.9
3 | 14.4 | 12 | 10.8 | 7.2 | 6 | 3

Parenteral drug products should be inspected visually for particulate matter and discoloration prior to administration whenever solution and container permit. Any unused solution should be discarded according to institutional procedures for antineoplastics.

2.4 Admixture Stability

Bendamustine Hydrochloride Injection contains no antimicrobial preservative. The admixture should be prepared as close as possible to the time of patient administration.

If diluted with 0.9% Sodium Chloride Injection, USP, or 2.5% Dextrose/0.45% Sodium Chloride Injection, USP, the final admixture is stable for 24 hours when stored refrigerated (2° to 8°C or 36° to 46°F) or for 3 hours when stored at room temperature (15° to 30°C or 59° to 86°F) and room light. Administration of diluted Bendamustine Hydrochloride Injection must be completed within this period of time.

Bendamustine Hydrochloride Injection is supplied in a multiple-dose vial. Retain the partially used vial in original package to protect from light and store refrigerated (2° to 8°C or 36° to 46°F) if additional dose withdrawal from the same vial is intended.

2.5 Stability of Partially Used Vials (Needle Punched Vials)

Bendamustine Hydrochloride Injection is supplied as a multiple-dose vial. Although it does not contain any antimicrobial preservative, Bendamustine Hydrochloride Injection is bacteriostatic. The partially used vials are stable for up to 28 days when stored in its original carton under refrigeration (2° to 8°C or 36° to 46°F). Each vial is not recommended for more than a total of six (6) dose withdrawals.

After first use, store the partially used vial in original carton at 2° to 8°C (36° to 46°F), and then discard after 28 days.

3 DOSAGE FORMS AND STRENGTHS

Injection: 100 mg/4 mL (25 mg/mL) as a clear and colorless to yellow solution in a multiple-dose vial.

4 CONTRAINDICATIONS

Bendamustine Hydrochloride Injection is contraindicated in patients with a known hypersensitivity (e.g., anaphylactic and anaphylactoid reactions) to bendamustine, polyethylene glycol 400, alcohol, or monothioglycerol. [see Warnings and Precautions (5.4)]

5 WARNINGS AND PRECAUTIONS

5.1 Myelosuppression

Bendamustine hydrochloride caused severe myelosuppression (Grade 3-4) in 98% of patients in the two NHL studies [see Adverse Reactions (6.1)]. Three patients (2%) died from myelosuppression-related adverse reactions; one each from neutropenic sepsis, diffuse alveolar hemorrhage with Grade 3 thrombocytopenia, and pneumonia from an opportunistic infection (CMV).

Bendamustine Hydrochloride Injection causes myelosuppression. Monitor complete blood counts, including leukocytes, platelets, hemoglobin (Hgb), and neutrophils frequently. In the clinical trials, blood counts were monitored every week initially. Hematologic nadirs were observed predominantly in the third week of therapy. Myelosuppression may require dose delays and/or subsequent dose reductions if recovery to the recommended values has not occurred by the first day of the next scheduled cycle. Prior to the initiation of the next cycle of therapy, the ANC should be ≥ 1 x 10^9 /L and the platelet count should be ≥ 75 x 10^9 /L [see Dosage and Administration (2.1) and (2.2)].

5.2 Infections

Infection, including pneumonia, sepsis, septic shock, hepatitis and death has occurred in adult and pediatric patients in clinical trials and in postmarketing reports for bendamustine hydrochloride [see Adverse Reactions (6.1)]. Patients with myelosuppression following treatment with bendamustine hydrochloride are more susceptible to infections. Advise patients with myelosuppression following Bendamustine Hydrochloride Injection treatment to contact a physician immediately if they have symptoms or signs of infection.

Patients treated with Bendamustine Hydrochloride Injection are at risk for reactivation of infections including (but not limited to) hepatitis B, cytomegalovirus, Mycobacterium tuberculosis, and herpes zoster. Patients should undergo appropriate measures (including clinical and laboratory monitoring, prophylaxis, and treatment) for infection and infection reactivation prior to administration.

5.3 Progressive Multifocal Leukoencephalopathy (PML)

Progressive multifocal leukoencephalopathy (PML), including fatal cases, have occurred following treatment with bendamustine, primarily in combination with rituximab or obinutuzumab [see Adverse Reactions (6.2)]. Consider PML in the differential diagnosis in patients with new or worsening neurological, cognitive or behavioral signs or symptoms. If PML is suspected, withhold Bendamustine Hydrochloride Injection treatment and perform appropriate diagnostic evaluations. Consider discontinuation or reduction of any concomitant chemotherapy or immunosuppressive therapy in patients who develop PML.

5.4 Anaphylaxis and Infusion Reactions

Infusion reactions to bendamustine hydrochloride have occurred commonly in clinical trials [see Adverse Reactions (6.1)]. Symptoms include fever, chills, pruritus and rash. In rare instances severe anaphylactic and anaphylactoid reactions have occurred, particularly in the second and subsequent cycles of therapy. Monitor clinically and discontinue drug for severe reactions. Ask patients about symptoms suggestive of infusion reactions after their first cycle of therapy. Patients who experience Grade 3 or worse allergic-type reactions should not be rechallenged. Consider measures to prevent severe reactions, including antihistamines, antipyretics and corticosteroids in subsequent cycles in patients who have experienced Grade 1 or 2 infusion reactions. Discontinue Bendamustine Hydrochloride Injection for patients with Grade 4 infusion reactions. Consider discontinuation for Grade 3 infusion reactions as clinically appropriate considering individual benefits, risks, and supportive care.

5.5 Tumor Lysis Syndrome

Tumor lysis syndrome associated with bendamustine hydrochloride has occurred in patients in clinical trials and in post-marketing reports [see Adverse Reactions (6.1)]. The onset tends to be within the first treatment cycle of bendamustine hydrochloride and, without intervention, may lead to acute renal failure and death. Preventive measures include vigorous hydration and close monitoring of blood chemistry, particularly potassium and uric acid levels. Allopurinol has also been used during the beginning of bendamustine hydrochloride therapy. However, there may be an increased risk of severe skin toxicity when bendamustine hydrochloride and allopurinol are administered concomitantly. [see Warnings and Precautions (5.6)].

5.6 Skin Reactions

Fatal and serious skin reactions have been reported with bendamustine hydrochloride treatment in clinical trials and postmarketing safety reports, including toxic skin reactions [Stevens-Johnson Syndrome (SJS), toxic epidermal necrolysis (TEN), and drug reaction with eosinophilia and systemic symptoms (DRESS), bullous exanthema, and rash [see Adverse Reactions (6.1 and 6.2)]. Events occurred when bendamustine hydrochloride was given as a single agent and in combination with other anticancer agents or allopurinol.

Where skin reactions occur, they may be progressive and increase in severity with further treatment. Monitor patients with skin reactions closely. If skin reactions are severe or progressive, withhold or discontinue Bendamustine Hydrochloride Injection.

5.7 Hepatotoxicity

Fatal and serious cases of liver injury have been reported with Bendamustine Hydrochloride Injection. Combination therapy, progressive disease or reactivation of hepatitis B were confounding factors in some patients. [see Warnings and Precautions (5.2)] Most cases were reported within the first three months of starting therapy. Monitor liver chemistry tests prior to and during Bendamustine Hydrochloride Injection therapy.

5.8 Other Malignancies

There are reports of pre-malignant and malignant diseases that have developed in patients who have been treated with bendamustine hydrochloride, including myelodysplastic syndrome, myeloproliferative disorders, acute myeloid leukemia, bronchial carcinoma, and non-melanoma skin cancer, including basal cell carcinoma and squamous cell carcinoma [see Adverse Reactions (6.2)].

Monitor patients for the development of secondary malignancies. Perform dermatologic evaluations during and after treatment with Bendamustine Hydrochloride Injection.

5.9 Extravasation Injury

Bendamustine hydrochloride extravasations have been reported in postmarketing resulting in hospitalizations from erythema, marked swelling, and pain [see Adverse Reactions (6.2)]. Assure good venous access prior to starting Bendamustine Hydrochloride Injection infusion and monitor the intravenous infusion site for redness, swelling, pain, infection, and necrosis during and after administration of Bendamustine Hydrochloride Injection.

5.10 Embryo-Fetal Toxicity

Based on findings from animal reproduction studies and the drug’s mechanism of action, Bendamustine Hydrochloride Injection can cause fetal harm when administered to a pregnant woman. Single intraperitoneal doses of bendamustine (that approximated the maximum recommended human dose based on body surface area) to pregnant mice and rats during organogenesis caused adverse developmental outcomes, including an increase in resorptions, skeletal and visceral malformations, and decreased fetal body weights.

Advise pregnant women of the potential risk to a fetus. Advise females of reproductive potential to use an effective method of contraception during treatment with Bendamustine Hydrochloride Injection and for 6 months after the last dose. Advise males with female partners of reproductive potential to use effective contraception during treatment with Bendamustine Hydrochloride Injection and for 3 months after the last dose [see Use in Specific Populations (8.1, 8.3) and Clinical Pharmacology (12.1)].

6 ADVERSE REACTIONS

The following clinically significant serious adverse reactions are discussed in greater detail in other sections of the prescribing information.

- Myelosuppression [see Warnings and Precautions (5.1)]
- Infections [see Warnings and Precautions (5.2)]
- Progressive Multifocal Leukoencephalopathy (PML) [see Warnings and Precautions (5.3)]
- Anaphylaxis and Infusion Reactions [see Warnings and Precautions (5.4)]
- Tumor Lysis Syndrome [see Warnings and Precautions (5.5)]
- Skin Reactions [see Warnings and Precautions (5.6)]
- Hepatotoxicity [see Warnings and Precautions (5.7)]
- Other Malignancies [see Warnings and Precautions (5.8)]
- Extravasation Injury [see Warnings and Precautions (5.9)]

6.1 Clinical Trials Experience

Because clinical trials are conducted under widely varying conditions, adverse reaction rates observed in the clinical trials of a drug cannot be directly compared to rates in the clinical trials of another drug and may not reflect the rates observed in practice.

Clinical Trials Experience in CLL

The data described below reflect exposure to bendamustine hydrochloride in 153 patients. Bendamustine hydrochloride was studied in an active-controlled, randomized trial. The population was 45-77 years of age, 63% male, 100% white, and had treatment naïve CLL. All patients started the study at a dose of 100 mg/m^2 intravenously over 30 minutes on Days 1 and 2 every 28 days.

Adverse reactions were reported according to NCI CTC v.2.0. In the randomized CLL clinical study, non-hematologic adverse reactions (any grade) in the bendamustine hydrochloride group that occurred with a frequency greater than 15% were pyrexia (24%), nausea (20%), and vomiting (16%).

Other adverse reactions seen frequently in one or more studies included asthenia, fatigue, malaise, and weakness; dry mouth; somnolence; cough; constipation; headache; mucosal inflammation and stomatitis.

Worsening hypertension was reported in 4 patients treated with bendamustine hydrochloride in the randomized CLL clinical study and in none treated with chlorambucil. Three of these 4 adverse reactions were described as a hypertensive crisis and were managed with oral medications and resolved.

The most frequent adverse reactions leading to study withdrawal for patients receiving bendamustine hydrochloride were hypersensitivity (2%) and pyrexia (1%).

Table 1 contains the treatment emergent adverse reactions, regardless of attribution, that were reported in ≥ 5% of patients in either treatment group in the randomized CLL clinical study.

Table 1: Non-Hematologic Adverse Reactions Occurring in Randomized CLL Clinical Study in at Least 5% of Patients
 | Number (%) of patients
 | Bendamustine Hydrochloride (N=153) |  | Chlorambucil (N=143)
Body System Adverse Reaction | All Grades | Grade 3/4 | All Grades | Grade 3/4
Total number of patients with at least 1 adverse reaction | 121 (79) | 52 (34) | 96 (67) | 25 (17)
Gastrointestinal disorders
Nausea | 31 (20) | 1 (<1) | 21 (15) | 1 (<1)
Vomiting | 24 (16) | 1 (<1) | 9 (6) | 0
Diarrhea | 14 (9) | 2 (1) | 5 (3) | 0
General disorders and administration site conditions
Pyrexia | 36 (24) | 6 (4) | 8 (6) | 2 (1)
Fatigue | 14 (9) | 2 (1) | 8 (6) | 0
Asthenia | 13 (8) | 0 | 6 (4) | 0
Chills | 9 (6) | 0 | 1 (<1) | 0
Immune system disorders
Hypersensitivity | 7 (5) | 2 (1) | 3 (2) | 0
Infections and infestations
Nasopharyngitis | 10 (7) | 0 | 12 (8) | 0
Infection | 9 (6) | 3 (2) | 1 (<1) | 1 (<1)
Herpes simplex | 5 (3) | 0 | 7 (5) | 0
Investigations
Weight decreased | 11 (7) | 0 | 5 (3) | 0
Metabolism and nutrition disorders
Hyperuricemia | 11 (7) | 3 (2) | 2 (1) | 0
Respiratory, thoracic and mediastinal disorders
Cough | 6 (4) | 1 (<1) | 7 (5) | 1 (<1)
Skin and subcutaneous tissue disorders
Rash | 12 (8) | 4 (3) | 7 (5) | 3 (2)
Pruritus | 8 (5) | 0 | 2 (1) | 0

The Grade 3 and 4 hematology laboratory test values by treatment group in the randomized CLL clinical study are described in Table 2. These findings confirm the myelosuppressive effects seen in patients treated with bendamustine hydrochloride. Red blood cell transfusions were administered to 20% of patients receiving bendamustine hydrochloride compared with 6% of patients receiving chlorambucil.

Table 2: Incidence of Hematology Laboratory Abnormalities in Patients Who Received Bendamustine Hydrochloride or Chlorambucil in the Randomized CLL Clinical Study
Laboratory Abnormality | Bendamustine Hydrochloride N=150 |  | Chlorambucil N=141
Laboratory Abnormality | All Grades n (%) | Grade 3/4 n (%) | All Grades n (%) | Grade 3/4 n (%)
Hemoglobin Decreased | 134 (89) | 20 (13) | 115 (82) | 12 (9)
Platelets Decreased | 116 (77) | 16 (11) | 110 (78) | 14 (10)
Leukocytes Decreased | 92 (61) | 42 (28) | 26 (18) | 4 (3)
Lymphocytes Decreased | 102 (68) | 70 (47) | 27 (19) | 6 (4)
Neutrophils Decreased | 113 (75) | 65 (43) | 86 (61) | 30 (21)

In the randomized CLL trial, 34% of patients had bilirubin elevations, some without associated significant elevations in AST and ALT. Grade 3 or 4 increased bilirubin occurred in 3% of patients. Increases in AST and ALT of Grade 3 or 4 were limited to 1% and 3% of patients, respectively. Patients treated with bendamustine hydrochloride may also have changes in their creatinine levels. If abnormalities are detected, monitoring of these parameters should be continued to ensure that further deterioration does not occur.

Clinical Trials Experience in NHL

The data described below reflect exposure to bendamustine hydrochloride in 176 patients with indolent B-cell NHL treated in two single-arm studies. The population was 31-84 years of age, 60% male, and 40% female. The race distribution was 89% White, 7% Black, 3% Hispanic, 1% other, and <1% Asian. These patients received bendamustine hydrochloride at a dose of 120 mg/m^2 intravenously on Days 1 and 2 for up to eight 21-day cycles.

The adverse reactions occurring in at least 5% of the NHL patients, regardless of severity, are shown in Table 3. The most common non-hematologic adverse reactions (≥30%) were nausea (75%), fatigue (57%), vomiting (40%), diarrhea (37%) and pyrexia (34%). The most common non-hematologic Grade 3 or 4 adverse reactions (≥5%) were fatigue (11%), febrile neutropenia (6%), and pneumonia, hypokalemia and dehydration, each reported in 5% of patients.

Table 3: Non-Hematologic Adverse Reactions Occurring in at Least 5% of NHL Patients Treated with Bendamustine Hydrochloride by System Organ Class and Preferred Term (N=176)
Body System | Number (%) of patientsError! Hyperlink reference not valid.
Adverse Reaction | All Grades | Grade 3/4
Total number of patients with at least 1 adverse reaction | 176 (100) | 94 (53)
Cardiac Disorders
Tachycardia | 13 (7) | 0
Gastrointestinal disorders
Nausea | 132 (75) | 7 (4)
Vomiting | 71 (40) | 5 (3)
Diarrhea | 65 (37) | 6 (3)
Constipation | 51 (29) | 1 (<1)
Stomatitis | 27 (15) | 1 (<1)
Abdominal pain | 22 (13) | 2 (1)
Dyspepsia | 20 (11) | 0
Gastroesophageal reflux disease | 18 (10) | 0
Dry mouth | 15 (9) | 1 (<1)
Abdominal pain upper | 8 (5) | 0
Abdominal distension | 8 (5) | 0
General disorders and administration site conditions
Fatigue | 101 (57) | 19 (11)
Pyrexia | 59 (34) | 3 (2)
Chills | 24 (14) | 0
Edema peripheral | 23 (13) | 1 (<1)
Asthenia | 19 (11) | 4 (2)
Chest pain | 11 (6) | 1 (<1)
Infusion site pain | 11 (6) | 0
Pain | 10 (6) | 0
Catheter site pain | 8 (5) | 0
Infections and infestations
Herpes zoster | 18 (10) | 5 (3)
Upper respiratory tract infection | 18 (10) | 0
Urinary tract infection | 17 (10) | 4 (2)
Sinusitis | 15 (9) | 0
Pneumonia | 14 (8) | 9 (5)
Febrile neutropenia | 11 (6) | 11 (6)
Oral candidiasis | 11 (6) | 2 (1)
Nasopharyngitis | 11 (6) | 0
Investigations
Weight decreased | 31 (18) | 3 (2)
Metabolism and nutrition disorders
Anorexia | 40 (23) | 3 (2)
Dehydration | 24 (14) | 8 (5)
Decreased appetite | 22 (13) | 1 (<1)
Hypokalemia | 15 (9) | 9 (5)
Musculoskeletal and connective tissue disorders
Back pain | 25 (14) | 5 (3)
Arthralgia | 11 (6) | 0
Pain in extremity | 8 (5) | 2 (1)
Bone pain | 8 (5) | 0
Nervous system disorders
Headache | 36 (21) | 0
Dizziness | 25 (14) | 0
Dysgeusia | 13 (7) | 0
Psychiatric disorder
Insomnia | 23 (13) | 0
Anxiety | 14 (8) | 1 (<1)
Depression | 10 (6) | 0
Respiratory, thoracic and mediastinal disorders
Cough | 38 (22) | 1 (<1)
Dyspnea | 28 (16) | 3 (2)
Pharyngolaryngeal pain | 14 (8) | 1 (<1)
Wheezing | 8 (5) | 0
Nasal congestion | 8 (5) | 0
Skin and subcutaneous tissue disorders
Rash | 28 (16) | 1 (<1)
Pruritus | 11 (6) | 0
Dry skin | 9 (5) | 0
Night sweats | 9 (5) | 0
Hyperhidrosis | 8 (5) | 0
Vascular disorders
Hypotension | 10 (6) | 2 (1)
*Patients may have reported more than 1 adverse reaction.
NOTE: Patients counted only once in each preferred term category and once in each system organ class category

Hematologic toxicities, based on laboratory values and CTC grade, in NHL patients treated in both single arm studies combined are described in Table 4. Clinically important chemistry laboratory values that were new or worsened from baseline and occurred in >1% of patients at Grade 3 or 4, in NHL patients treated in both single arm studies combined were hyperglycemia (3%), elevated creatinine (2%), hyponatremia (2%), and hypocalcemia (2%).

Table 4: Incidence of Hematology Laboratory Abnormalities in Patients Who Received Bendamustine Hydrochloride in the NHL Studies
Hematology Variable | Percent of Patients
Hematology Variable | All Grades | Grade 3/4
Lymphocytes Decreased | 99 | 94
Leukocytes Decreased | 94 | 56
Hemoglobin Decreased | 88 | 11
Neutrophils Decreased | 86 | 60
Platelets Decreased | 86 | 25

In both studies, serious adverse reactions, regardless of causality, were reported in 37% of patients receiving bendamustine hydrochloride. The most common serious adverse reactions occurring in ≥5% of patients were febrile neutropenia and pneumonia. Other important serious adverse reactions reported in clinical trials and/or post-marketing experience were acute renal failure, cardiac failure, hypersensitivity, skin reactions, pulmonary fibrosis, and myelodysplastic syndrome.

Serious drug-related adverse reactions reported in clinical trials included myelosuppression, infection, pneumonia, tumor lysis syndrome and infusion reactions. Adverse reactions occurring less frequently but possibly related to bendamustine hydrochloride treatment were hemolysis, dysgeusia/taste disorder, atypical pneumonia, sepsis, herpes zoster, erythema, dermatitis, and skin necrosis.

6.2 Postmarketing Experience

The following adverse reactions have been identified during post-approval use of bendamustine hydrochloride. Because these reactions are reported voluntarily from a population of uncertain size, it is not always possible to reliably estimate their frequency or establish a causal relationship to drug exposure.

Blood and lymphatic systems disorders: Pancytopenia

Cardiovascular disorders: Atrial fibrillation, congestive heart failure (some fatal), myocardial infarction (some fatal), palpitation

General disorders and administration site conditions: Injection site reactions (including phlebitis, pruritus, irritation, pain, swelling), infusion site reactions (including phlebitis, pruritus, irritation, pain, swelling)

Immune system disorders: Anaphylaxis

Infections and infestations: Pneumocystis jirovecii pneumonia, progressive multifocal leukoencephalopathy (PML)

Renal and urinary disorders: Nephrogenic diabetes insipidus (NDI)

Respiratory, thoracic and mediastinal disorders: Pneumonitis

Skin and subcutaneous tissue disorders: Drug reaction with eosinophilia and systemic symptoms (DRESS), non-melanoma skin cancer (NMSC), Stevens-Johnson syndrome (SJS), Toxic epidermal necrolysis (TEN).

7 DRUG INTERACTIONS

7.1 Effect of Other Drugs on Bendamustine Hydrochloride Injection

CYP1A2 Inhibitors
The coadministration of Bendamustine Hydrochloride Injection with CYP1A2 inhibitors may increase bendamustine plasma concentrations and may result in increased incidence of adverse reactions with Bendamustine Hydrochloride Injection [see Clinical Pharmacology (12.3)]. Consider alternative therapies that are not CYP1A2 inhibitors during treatment with Bendamustine Hydrochloride Injection.

CYP1A2 Inducers
The coadministration of Bendamustine Hydrochloride Injection with CYP1A2 inducers may decrease bendamustine plasma concentrations and may result in decreased efficacy of Bendamustine Hydrochloride Injection [see Clinical Pharmacology (12.3)]. Consider alternative therapies that are not CYP1A2 inducers during treatment with Bendamustine Hydrochloride Injection.

8 USE IN SPECIFIC POPULATIONS

8.1 Pregnancy

Risk Summary

In animal reproduction studies, intraperitoneal administration of bendamustine to pregnant mice and rats during organogenesis at doses 0.6 to 1.8 times the maximum recommended human dose (MRHD) resulted in embryo-fetal and/or infant mortality, structural abnormalities, and alterations to growth (see Data). There are no available data on bendamustine hydrochloride use in pregnant women to evaluate for a drug-associated risk of major birth defects, miscarriage or adverse maternal or fetal outcomes. Advise pregnant women of the potential risk to a fetus.

The estimated background risk of major birth defects and miscarriage for the indicated population is unknown. All pregnancies have a background risk of birth defect, loss, or other adverse outcomes. In the U.S. general population, the estimated background risk of major birth defects and miscarriage in clinically recognized pregnancies is 2% to 4% and 15% to 20%, respectively.

Data

Animal Data

Bendamustine hydrochloride was intraperitoneally administered once to mice from 210 mg/m^2 (approximately 1.8 times the MRHD) during organogenesis and caused an increase in resorptions, skeletal and visceral malformations (exencephaly, cleft palates, accessory rib, and spinal deformities) and decreased fetal body weights. This dose did not appear to be maternally toxic and lower doses were not evaluated. Repeat intraperitoneal administration of bendamustine hydrochloride in mice on gestation days 7 to 11 resulted in an increase in resorptions from 75 mg/m^2 (approximately 0.6 times the MRHD) and an increase in abnormalities from 112.5 mg/m^2 (approximately 0.9 times the MRHD), similar to those seen after a single intraperitoneal administration.

Bendamustine hydrochloride was intraperitoneally administered once to rats from 120 mg/m^2 (approximately the MRHD) on gestation days 4, 7, 9, 11, or 13 and caused embryo and fetal lethality as indicated by increased resorptions and a decrease in live fetuses. A significant increase in external (effect on tail, head, and herniation of external organs [exomphalos]) and internal (hydronephrosis and hydrocephalus) malformations were seen in dosed rats.

8.2 Lactation

Risk Summary

There are no data on the presence of bendamustine hydrochloride or its metabolites in either human or animal milk, the effects on the breastfed child, or the effects on milk production. Because of the potential for serious adverse reactions in the breastfed child, advise women not to breastfeed during treatment with Bendamustine Hydrochloride Injection, and for 1 week after the last dose.

8.3 Females and Males of Reproductive Potential

Bendamustine Hydrochloride Injection can cause embryo-fetal harm when administered to a pregnant woman [see Use in Specific Populations (8.1)].

Pregnancy Testing

Pregnancy testing is recommended for females of reproductive potential prior to initiation of treatment with Bendamustine Hydrochloride Injection.

Contraception

Females

Advise female patients of reproductive potential to use effective contraception during treatment with Bendamustine Hydrochloride Injection and for 6 months after the last dose.

Males

Based on genotoxicity findings, advise males with female partners of reproductive potential to use effective contraception during treatment with Bendamustine Hydrochloride Injection and for 3 months after the last dose [see Nonclinical Toxicology (13.1)].

Infertility

Based on findings from clinical studies, Bendamustine Hydrochloride Injection may impair male fertility. Impaired spermatogenesis, azoospermia, and total germinal aplasia have been reported in male patients treated with alkylating agents, especially in combination with other drugs. In some instances, spermatogenesis may return in patients in remission, but this may occur only several years after intensive chemotherapy has been discontinued. Advise patients of the potential risk to their reproductive capacities.

Based on findings from animal studies, Bendamustine Hydrochloride Injection may impair male fertility due to an increase in morphologically abnormal spermatozoa. The long-term effects of Bendamustine Hydrochloride Injection on male fertility, including the reversibility of adverse effects, have not been studied [see Nonclinical Toxicology (13.1)].

8.4 Pediatric Use

Safety and effectiveness in pediatric patients have not been established.

Safety, pharmacokinetics and efficacy were assessed in a single open-label trial (NCT01088984) in patients aged 1 to 19 years with relapsed or refractory acute leukemia, including 27 patients with acute lymphocytic leukemia (ALL) and 16 patients with acute myeloid leukemia (AML). Bendamustine hydrochloride was administered as an intravenous infusion over 60 minutes on Days 1 and 2 of each 21-day cycle. There was no treatment response (CR+ CRp) in any patient. The safety profile in these patients was consistent with that seen in adults, and no new safety signals were identified.

The pharmacokinetics of bendamustine in 43 patients, aged 1 to 19 years (median age of 10 years) were within range of values previously observed in adults given the same dose based on body surface area.

8.5 Geriatric Use

No overall differences in safety were observed between patients ≥65 years of age and younger patients. Efficacy was lower in patients 65 and over with CLL receiving bendamustine hydrochloride based upon an overall response rate of 47% for patients 65 and over and 70% for younger patients. Progression free survival was also longer in younger patients with CLL receiving bendamustine (19 months vs. 12 months). No overall differences in efficacy in patients with non-Hodgkin Lymphoma were observed between geriatric patients and younger patients.

8.6 Renal Impairment

Do not use Bendamustine Hydrochloride Injection in patients with creatinine clearance (CLcr) < 30 mL/min [see Clinical Pharmacology (12.3)].

8.7 Hepatic Impairment

Do not use Bendamustine Hydrochloride Injection in patients with AST or ALT 2.5-10 × upper limit of normal (ULN) and total bilirubin 1.5-3 × ULN, or total bilirubin > 3 × ULN [see Clinical Pharmacology (12.3)]

10 OVERDOSAGE

The intravenous LD50 of bendamustine hydrochloride is 240 mg/m^2 in the mouse and rat. Toxicities included sedation, tremor, ataxia, convulsions and respiratory distress.

Across all clinical experience, the reported maximum single dose received was 280 mg/m^2. Three of four patients treated at this dose showed ECG changes considered dose-limiting at 7 and 21 days post-dosing. These changes included QT prolongation (one patient), sinus tachycardia (one patient), ST and T wave deviations (two patients) and left anterior fascicular block (one patient). Cardiac enzymes and ejection fractions remained normal in all patients.

No specific antidote for bendamustine hydrochloride overdose is known. Management of overdosage should include general supportive measures, including monitoring of hematologic parameters and ECGs.

11 DESCRIPTION

Bendamustine hydrochloride is an alkylating agent. The chemical name of bendamustine hydrochloride is 1H-benzimidazole-2-butanoic acid, 5-[bis(2-chloroethyl)amino]1-methyl-, monohydrochloride. Its empirical molecular formula is C16H21Cl2N3O2∙HCl, and the molecular weight is 394.7. Bendamustine hydrochloride contains a mechlorethamine group and a benzimidazole heterocyclic ring with a butyric acid substituent, and has the following structural formula:

Bendamustine Hydrochloride Injection for intravenous use is supplied as a sterile, clear, and colorless to yellow solution in a multiple-dose clear glass vial. Each milliliter contains 25 mg of bendamustine hydrochloride (equivalent to 22.7 mg bendamustine free base), 0.1 g of alcohol, USP (equivalent to 0.1 g absolute ethanol), 5 mg of monothioglycerol, NF (used as an antioxidant) and q.s. to 1 mL polyethylene glycol 400, NF. Sodium hydroxide, NF is used to adjust the acidity of polyethylene glycol 400.

12 CLINICAL PHARMACOLOGY

12.1 Mechanism of Action

Bendamustine is a bifunctional mechlorethamine derivative containing a purine-like benzimidazole ring. Mechlorethamine and its derivatives form electrophilic alkyl groups. These groups form covalent bonds with electron-rich nucleophilic moieties, resulting in interstrand DNA crosslinks. The bifunctional covalent linkage can lead to cell death via several pathways. Bendamustine is active against both quiescent and dividing cells. The exact mechanism of action of bendamustine remains unknown.

12.2 Pharmacodynamics

Based on the pharmacokinetics/pharmacodynamics analyses of data from adult NHL patients, nausea increased with increasing bendamustine Cmax.

Cardiac Electrophysiology
The effect of bendamustine on the QTc interval was evaluated in 53 patients with indolent NHL and mantle cell lymphoma on Day 1 of Cycle 1 after administration of rituximab at 375 mg/m^2 intravenous infusion followed by a 30-minute intravenous infusion of bendamustine at 90 mg/m^2/day. No mean changes greater than 20 milliseconds were detected up to one hour post infusion. The potential for delayed effects on the QT interval after one hour was not evaluated.

12.3 Pharmacokinetics

Absorption

Following a single intravenous dose of bendamustine hydrochloride Cmax typically occurred at the end of infusion. The dose proportionality of bendamustine has not been studied.

Distribution

The protein binding of bendamustine ranged from 94 to 96% and was concentration independent from 1 to 50 μg/mL. The blood to plasma concentration ratios in human blood ranged from 0.84 to 0.86 over a concentration range of 10 to 100 μg/mL.

The mean steady-state volume of distribution (Vss) of bendamustine was approximately 20 to 25 L.

Elimination

After a single intravenous dose of 120 mg/m^2 of bendamustine over 1 hour, the intermediate half-life (t½) of the parent compound is approximately 40 minutes. The mean terminal elimination t½ of two active metabolites, γ-hydroxybendamustine (M3) and N-desmethylbendamustine (M4) are approximately 3 hours and 30 minutes, respectively. Bendamustine clearance in humans is approximately 700 mL/min.

Metabolism

Bendamustine is extensively metabolized via hydrolytic, oxidative, and conjugative pathways. Bendamustine is primarily metabolized via hydrolysis to monohydroxy (HP1) and dihydroxy-bendamustine (HP2) metabolites with low cytotoxic activity in vitro. Two active minor metabolites, M3 and M4, are primarily formed via CYP1A2 in vitro. M3 and M4 concentrations of these metabolites in plasma are 1/10th and 1/100th that of the parent compound, respectively.

Excretion

Following intravenous infusion of radiolabeled bendamustine hydrochloride in cancer patients, approximately 76% of the dose was recovered. Approximately 50% of the dose was recovered in the urine (3.3% unchanged) and approximately 25% of the dose was recovered in the feces. Less than 1% of the dose was recovered in the urine as M3 and M4, and less than 5% of the dose was recovered in the urine as HP2.

Specific Populations

No clinically meaningful effects on the pharmacokinetics of bendamustine were observed based on age (31 to 84 years), sex, mild to moderate renal impairment (CLcr ≥ 30 mL/min), or hepatic impairment with total bilirubin 1.5 < ULN and AST or ALT < 2.5 × ULN. The effects of severe renal impairment (CLcr < 30 mL/min), or hepatic impairment with total bilirubin 1.5-3 × ULN and AST or ALT 2.5-10 × ULN or total bilirubin > 3 × ULN on the pharmacokinetics of bendamustine is unknown.

Race/Ethnicity

Exposures in Japanese subjects (n=6) were 40% higher than that in non-Japanese subjects receiving the same dose. The clinical importance of this difference on the safety and efficacy of bendamustine hydrochloride in Japanese subjects has not been established.

Drug Interaction Studies

In Vitro Studies

Effect of Bendamustine on CYP Substrates

Bendamustine did not inhibit CYP1A2, 2C9/10, 2D6, 2E1, or 3A4/5. Bendamustine did not induce metabolism of CYP1A2, CYP2A6, CYP2B6, CYP2C8, CYP2C9, CYP2C19, CYP2E1, or CYP3A4/5.

Effect of Transporters on Bendamustine Hydrochloride

Bendamustine is a substrate of P-glycoprotein and breast cancer resistance protein (BCRP).

13 NONCLINICAL TOXICOLOGY

13.1 Carcinogenesis, Mutagenesis, Impairment of Fertility

Bendamustine was carcinogenic in mice. After intraperitoneal injections at 37.5 mg/m^2/day (the lowest dose tested, approximately 0.3 times the maximum recommended human dose [MRHD]) and 75 mg/m^2/day (approximately 0.6 times the MRHD) for 4 days, peritoneal sarcomas in female AB/jena mice were produced. Oral administration at 187.5 mg/m^2/day (the only dose tested, approximately 1.6 times the MRHD) for 4 days induced mammary carcinomas and pulmonary adenomas.

Bendamustine is a mutagen and clastogen. In a reverse bacterial mutation assay (Ames assay), bendamustine was shown to increase revertant frequency in the absence and presence of metabolic activation. Bendamustine was clastogenic in human lymphocytes in vitro, and in rat bone marrow cells in vivo (increase in micronucleated polychromatic erythrocytes) from 37.5 mg/m^2, (the lowest dose tested, approximately 0.3 times the MRHD).

Bendamustine induced morphologic abnormalities in spermatozoa in mice. Following tail vein injection of bendamustine at 120 mg/m^2 or a saline control on days 1 and 2 for a total of three weeks, the number of spermatozoa with morphologic abnormalities was 16% higher in the bendamustine-treated group as compared to the saline control group.

14 CLINICAL STUDIES

14.1 Chronic Lymphocytic Leukemia (CLL)

The safety and efficacy of bendamustine hydrochloride were evaluated in an open-label, randomized, controlled multicenter trial comparing bendamustine hydrochloride to chlorambucil. The trial was conducted in 301 previously-untreated patients with Binet Stage B or C (Rai Stages I - IV) CLL requiring treatment. Need-to-treat criteria included hematopoietic insufficiency, B-symptoms, rapidly progressive disease or risk of complications from bulky lymphadenopathy. Patients with autoimmune hemolytic anemia or autoimmune thrombocytopenia, Richter’s syndrome, or transformation to prolymphocytic leukemia were excluded from the study.

The patient populations in the bendamustine hydrochloride and chlorambucil treatment groups were balanced with regard to the following baseline characteristics: age (median 63 vs. 66 years), gender (63% vs. 61% male), Binet stage (71% vs. 69% Binet B), lymphadenopathy (79% vs. 82%), enlarged spleen (76% vs. 80%), enlarged liver (48% vs. 46%), hypercellular bone marrow (79% vs. 73%), “B” symptoms (51% vs. 53%), lymphocyte count (mean 65.7x10^9/L vs. 65.1x10^9/L), and serum lactate dehydrogenase concentration (mean 370.2 vs. 388.4 U/L). Ninety percent of patients in both treatment groups had immuno-phenotypic confirmation of CLL (CD5, CD23 and either CD19 or CD20 or both).

Patients were randomly assigned to receive either bendamustine hydrochloride at 100 mg/m^2, administered intravenously over a period of 30 minutes on Days 1 and 2 or chlorambucil at 0.8 mg/kg (Broca’s normal weight) administered orally on Days 1 and 15 of each 28-day cycle. Efficacy endpoints of objective response rate and progression-free survival were calculated using a pre-specified algorithm based on NCI working group criteria for CLL.

The results of this open-label randomized study demonstrated a higher rate of overall response and a longer progression-free survival for bendamustine hydrochloride compared to chlorambucil (see Table 5). Survival data are not mature.

Table 5: Efficacy Data for CLL
 | Bendamustine Hydrochloride (N=153) | Chlorambucil (N=148) | p-value
Response Rate n (%)
Overall response rate | 90 (59) | 38 (26) | <0.0001
(95% CI) | (51, 66.6) | (18.6, 32.7)
Complete response (CR)Error! Hyperlink reference not valid. | 13 (8) | 1 (<1)
Nodular partial response (nPR)Error! Hyperlink reference not valid. | 4 (3) | 0
Partial response (PR) Error! Hyperlink reference not valid. | 73 (48) | 37 (25)
Progression-Free Survival Error! Hyperlink reference not valid.
Median, months (95% CI) | 18 (11.7, 23.5) | 6 (5.6, 8.6)
Hazard ratio (95% CI) | 0.27 (0.17, 0.43) |  | <0.0001
CI = confidence interval
* CR was defined as peripheral lymphocyte count ≤ 4 x 10^9/L, neutrophils ≥ 1.5 x 10^9/L, platelets >100 x 10^9/L, hemoglobin > 110g/L, without transfusions, absence of palpable hepatosplenomegaly, lymph nodes ≤ 1.5 cm, < 30% lymphocytes without nodularity in at least a normocellular bone marrow and absence of “B” symptoms. The clinical and laboratory criteria were required to be maintained for a period of at least 56 days.
** nPR was defined as described for CR with the exception that the bone marrow biopsy shows persistent nodules.
† PR was defined as ≥50% decrease in peripheral lymphocyte count from the pretreatment baseline value, and either ≥50% reduction in lymphadenopathy, or ≥50% reduction in the size of spleen or liver, as well as one of the following hematologic improvements: neutrophils ≥ 1.5 x 10^9/L or 50% improvement over baseline, platelets >100 x 10^9/L or 50% improvement over baseline, hemoglobin >110g/L or 50% improvement over baseline without transfusions, for a period of at least 56 days.
†† PFS was defined as time from randomization to progression or death from any cause.

Kaplan-Meier estimates of progression-free survival comparing bendamustine hydrochloride with chlorambucil are shown in Error! Hyperlink reference not valid..

Figure 1. Progression-Free Survival

14.2 Non-Hodgkin Lymphoma (NHL)

The efficacy of bendamustine hydrochloride was evaluated in a single arm study of 100 patients with indolent B-cell NHL that had progressed during or within six months of treatment with rituximab or a rituximab-containing regimen. Patients were included if they relapsed within 6 months of either the first dose (monotherapy) or last dose (maintenance regimen or combination therapy) of rituximab. All patients received bendamustine hydrochloride intravenously at a dose of 120 mg/m^2, on Days 1 and 2 of a 21-day treatment cycle. Patients were treated for up to 8 cycles.

The median age was 60 years, 65% were male, and 95% had a baseline WHO performance status of 0 or 1. Major tumor subtypes were follicular lymphoma (62%), diffuse small lymphocytic lymphoma (21%), and marginal zone lymphoma (16%). Ninety-nine percent of patients had received previous chemotherapy, 91% of patients had received previous alkylator therapy, and 97% of patients had relapsed within 6 months of either the first dose (monotherapy) or last dose (maintenance regimen or combination therapy) of rituximab.

Efficacy was based on the assessments by a blinded independent review committee (IRC) and included overall response rate (complete response + complete response unconfirmed + partial response) and duration of response (DR) as summarized in Table 6.

Table 6: Efficacy Data for NHLError! Hyperlink reference not valid.
 | Bendamustine Hydrochloride (N=100)
Response Rate (%)
Overall response rate (CR+CRu+PR) | 74
(95% CI) | (64.3, 82.3)
Complete response (CR) | 13
Complete response unconfirmed (CRu) | 4
Partial response (PR) | 57
Duration of Response (DR)
Median, months (95% CI) | 9.2 months (7.1, 10.8)
CI = confidence interval
*IRC assessment was based on modified International Working Group response criteria (IWG-RC). Modifications to IWG-RC specified that a persistently positive bone marrow in patients who met all other criteria for CR would be scored as PR. Bone marrow sample lengths were not required to be ≥20 mm.

15 REFERENCES

1. OSHA Hazardous Drugs. OSHA. [https://www.osha.gov/hazardous-drugs]

16 HOW SUPPLIED/STORAGE AND HANDLING

Safe Handling and Disposal

Bendamustine Hydrochloride Injection is a hazardous drug. Follow applicable special handling and disposal procedures^1. Care should be exercised in the handling and preparation of solutions prepared from Bendamustine Hydrochloride Injection. The use of gloves and safety glasses is recommended to avoid exposure in case of breakage of the vial or other accidental spillage. If gloves come in contact with Bendamustine Hydrochloride Injection prior to dilution, remove gloves and follow disposal procedures^1. If a solution of Bendamustine Hydrochloride Injection contacts the skin, wash the skin immediately and thoroughly with soap and water. If Bendamustine Hydrochloride Injection contacts the mucous membranes, flush thoroughly with water.

How Supplied

Bendamustine Hydrochloride Injection is supplied in individual cartons of 6 mL clear multiple-dose vials containing 100 mg of bendamustine hydrochloride as a clear and colorless to yellow solution.

NDC 10019-079-01, 100 mg/4 mL (25 mg/mL).

Storage

Store Bendamustine Hydrochloride Injection in refrigerator, 2° to 8°C (36° to 46°F). Retain vial in original carton until contents are used to protect from light.

17 PATIENT COUNSELING INFORMATION

Myelosuppression
Inform patients of the likelihood that Bendamustine Hydrochloride Injection will cause a decrease in white blood cells, platelets, and red blood cells and the need for frequent monitoring of blood counts. Advise patients to report shortness of breath, significant fatigue, bleeding, fever, or other signs of infection. [see Warnings and Precautions (5.1)]

Progressive Multifocal Leukoencephalopathy (PML)
Inform patients to immediately contact their healthcare provider if they experience confusion, memory loss, trouble thinking, difficulty talking or walking, vision loss or other neurological or cognitive symptoms [see Warnings and Precautions (5.3)].

Anaphylaxis and Infusion Reactions
Inform patients of the possibility of serious or mild allergic reactions and to immediately report rash, facial swelling, or difficulty breathing during or soon after infusion. [see Warnings and Precautions (5.4)]

Skin Reactions
Advise patients that a rash or itching may occur during treatment with Bendamustine Hydrochloride Injection. Advise patients to immediately report severe or worsening rash or itching. [see Warnings and Precautions (5.6)].

Hepatotoxicity
Inform patients of the possibility of developing liver function abnormalities and serious hepatic toxicity. Advise patients to immediately contact their health care provider if signs of liver failure occur, including jaundice, anorexia, bleeding or bruising. [see Warnings and Precautions (5.7)].

Fatigue
Advise patients that Bendamustine Hydrochloride Injection may cause tiredness and to avoid driving any vehicle or operating any dangerous tools or machinery if they experience this side effect. [see Adverse Reactions (6.1)]

Nausea and Vomiting
Advise patients that Bendamustine Hydrochloride Injection may cause nausea and/or vomiting. Patients should report nausea and vomiting so that symptomatic treatment may be provided. [see Adverse Reactions (6.1)]

Diarrhea
Advise patients that Bendamustine Hydrochloride Injection may cause diarrhea. Patients should report diarrhea to the physician so that symptomatic treatment may be provided. [see Adverse Reactions (6.1)]

Non-melanoma Skin Cancer (NMSC)
Advise patients to undergo regular skin cancer screenings, and to report any suspicious skin changes to their healthcare provider. [see Warnings and Precautions (5.8)]

Embryo-Fetal Toxicity

Advise pregnant women and females of reproductive potential of the potential risk to a fetus. Advise females to inform their healthcare provider of a known or suspected pregnancy [see Warnings and Precautions (5.10), Use in Specific Populations (8.1, 8.3), and Nonclinical Toxicology (13.1)].

Advise female patients of reproductive potential to use effective contraception during treatment with Bendamustine Hydrochloride Injection and for 6 months after the last dose [see Use in Specific Populations (8.1, 8.3)].

Advise males with female partners of reproductive potential to use effective contraception during treatment with Bendamustine Hydrochloride Injection and for 3 months after the last dose [see Use in Specific Populations (8.3) and Nonclinical Toxicology (13.1)].

Lactation

Advise females not to breastfeed during treatment with Bendamustine Hydrochloride Injection and for 1 week after the last dose [see Use in Specific Populations (8.2)].

Infertility

Advise males of reproductive potential that Bendamustine Hydrochloride Injection may impair fertility [see Use in Specific Populations (8.3)].

Manufactured for:

Baxter Healthcare Corporation
Deerfield, IL 60015, USA
1-866-888-2472
www.baxter.com

Made in Germany.

HA-30-02-393

Baxter in a registered trademark of Baxter International Inc.

PRINCIPAL DISPLAY PANEL

Container Label

Lot:
Exp:

NDC 10019-079-01
Sterile

Multiple-Dose Vial
Rx Only

Bendamustine HCl Injection
100 mg/4 mL (25 mg/mL)

Must dilute required dose in a
500 mL admixture prior to administration
For Intravenous Infusion Only

USA HA-65-02-315 C 666

Bar Code
3 10019 07901 1

Store in refrigerator,
2° to 8°C (36° to 46°F).
Retain vial in original carton until
contents are used to protect from light.
Dosage: See Prescribing Information.
Manufactured for:
Baxter Healthcare Corp.
DeerField, IL 60015, USA
Product of Germany

2D Bar Code

PEEL
HERE

Bendamustine HCl Injection 100 mg/4 mL (25 mg/mL)

CAUTION: Concentrate Solution – 25 mg/mL

Must be diluted prior to administration (see Prescribing Information for instructions)

Aseptically withdraw the volume needed for the required dose based on 25 mg/mL
concentration as per Table A (see Prescribing Information) and immediately transfer to a
500 mL infusion bag of 0.9% Sodium Chloride Injection or 2.5% Dextrose/
0.45% Sodium Chloride Injection. Do not use if solid or particulate matter is observed

Carton Label

Bendamustine HCl Injection
100 mg/4 mL (25 mg/mL)

Bar Code

NDC 10019-079-01
Sterile

Rx Only

Bendamustine HCl
Injection

100 mg/4 mL
(25 mg/mL)

For Intravenous Infusion Only

Must dilute required dose in a
500 mL infusion bag of 0.9%
Sodium Chloride Injection or
2.5% Dextrose/0.45% Sodium
Chloride Injection prior to
administration.

Manufactured for:
Baxter Healthcare Corporation
Deerfield, IL 60015, USA

Product of Germany

Baxter Logo

HA-80-03-226
USA

Store in refrigerator,
2° to 8°C (36° to 46°F).

Retain vial in original carton
until contents are used to
protect from light.

Dosage: See Prescribing
Information.

Each mL contains 25 mg
bendamustine hydrochloride
(equivalent to 22.7 mg
bendamustine free base),
0.1 g alcohol, USP (equivalent to
0.1 g absolute ethanol), 5 mg
monothioglycerol, NF in polyethylene
glycol 400, NF, sodium hydroxide,
NF to adjust acidity of polyethylene
glycol 400.

C
377

NDC 10019-079-01
Sterile

Rx Only

Bendamustine HCl
Injection

100 mg/4 mL
(25 mg/mL)

For Intravenous Infusion Only

Must dilute required dose in a
500 mL infusion bag of 0.9%
Sodium Chloride Injection or
2.5% Dextrose/0.45% Sodium
Chloride Injection prior to
administration.

One 4 mL Multiple-Dose Vial

2395b0105
Bar Code

Hazardous Agent - Use caution
during handling and preparation.
Use of gloves and safety glasses
is recommended to avoid
exposure. See Prescribing
Information for details.

Bar Code
(01)20310019079015